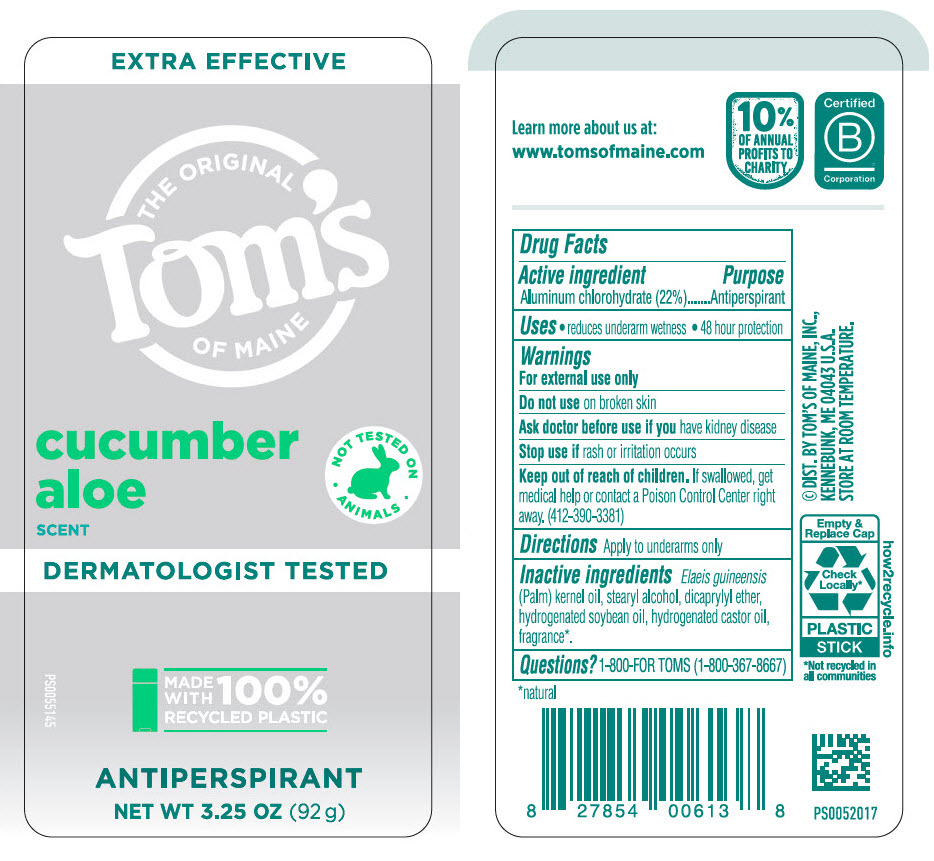 DRUG LABEL: Toms of Maine Toms of Maine Cucumber Aloe AP wo Olea
NDC: 51009-856 | Form: STICK
Manufacturer: Toms of Maine, Inc.
Category: otc | Type: HUMAN OTC DRUG LABEL
Date: 20260128

ACTIVE INGREDIENTS: ALUMINUM CHLOROHYDRATE 220 mg/1 g
INACTIVE INGREDIENTS: PALM KERNEL OIL; STEARYL ALCOHOL; DICAPRYLYL ETHER; HYDROGENATED SOYBEAN OIL; HYDROGENATED CASTOR OIL

Toms of Maine Tom's of Maine Cucumber Aloe AP wo Olea

Drug Facts

Active ingredient

Aluminum chlorohydrate (22%)

Purpose

Antiperspirant

Uses

- reduces underarm wetness
- 48 hour protection

Warnings

For external use only

Do not use on broken skin

Ask doctor before use if you have kidney disease

Stop use if rash or irritation occurs

Keep out of reach of children. If swallowed, get medical help or contact a Poison Control Center right away. (412-390-3381)

Directions

Apply to underarms only

Inactive ingredients

Elaeis guineensis (Palm) kernel oil, stearyl alcohol, dicaprylyl ether, hydrogenated soybean oil, hydrogenated castor oil, fragrance [natural] .

Questions?

1-800-FOR TOMS (1-800-367-8667)

© DIST. BY TOM'S OF MAINE, INC.,
KENNEBUNK, ME 04043 U.S.A.

PRINCIPAL DISPLAY PANEL - 92 g Container Label

EXTRA EFFECTIVE

THE ORIGINAL
Tom's
OF MAINE

cucumber
aloe
SCENT

NOT TESTED ON
• ANIMALS •

DERMATOLOGIST TESTED

PS0055145

MADE
WITH 100%
RECYCLED PLASTIC

ANTIPERSPIRANT

NET WT 3.25 OZ (92 g)